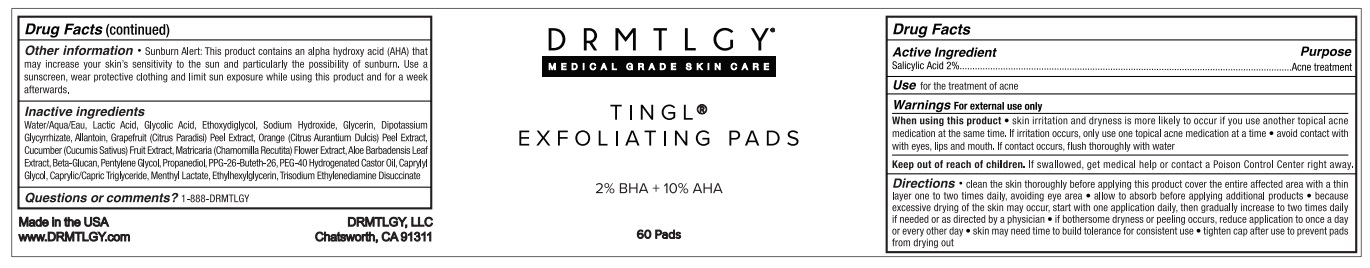 DRUG LABEL: TINGL EXFOLIATING PADS
NDC: 83286-011 | Form: CLOTH
Manufacturer: Drmtlgy, LLC
Category: otc | Type: HUMAN OTC DRUG LABEL
Date: 20250408

ACTIVE INGREDIENTS: SALICYLIC ACID 2 g/100 g
INACTIVE INGREDIENTS: WATER; LACTIC ACID, UNSPECIFIED FORM; GLYCOLIC ACID; DIETHYLENE GLYCOL MONOETHYL ETHER; SODIUM HYDROXIDE; GLYCERIN; GLYCYRRHIZINATE DIPOTASSIUM; ALLANTOIN; GRAPEFRUIT PEEL; ORANGE PEEL; CUCUMBER; CHAMOMILE; ALOE VERA LEAF; YEAST .BETA.-D-GLUCAN; PENTYLENE GLYCOL; PROPANEDIOL; PPG-26-BUTETH-26; POLYOXYL 40 HYDROGENATED CASTOR OIL; CAPRYLYL GLYCOL; MEDIUM-CHAIN TRIGLYCERIDES; MENTHYL LACTATE, (-)-; ETHYLHEXYLGLYCERIN; TRISODIUM ETHYLENEDIAMINE DISUCCINATE

DRMTLGY® TINGL® EXFOLIATING PADS

Active Ingredient

Salicylic Acid 2%

Purpose

Acne treatment

Use

for the treatment of acne

Warnings

For external use only

When using this product • skin irritation and dryness is more likely to occur if you use another topical acne medication at the same time. If irritation occurs, only use one topical acne medication at a time • avoid contact with eyes, lips and mouth. If contact occurs, flush thoroughly with water

Keep out of reach of children. If swallowed, get medical help or contact a Poison Control Center right away.

Directions

• clean the skin thoroughly before applying this product cover the entire affected area with a thin layer one to two times daily, avoiding eye area . • allow to absorb before applying additional products • because excessive drying of the skin may occur, start with one application daily, then gradually increase to two times daily if needed or as directed by a physician • if bothersome dryness or peeling occurs, reduce application to once a day or every other day • skin may need time to build tolerance for consistent use • tighten cap after use to prevent pads from drying out

Other information

• Sunburn Alert: This product contains an alpha hydroxy acid (AHA) that may increase your skin's sensitivity to the sun and particularly the possibility of sunburn. Use a sunscreen, wear protective clothing and limit sun exposure while using this product and for a week afterwards.

Inactive ingredients

Water/Aqua/Eau, Lactic Acid, Glycolic Acid, Ethoxydiglycol, Sodium Hydroxide, Glycerin, Dipotassium Glycyrrhizate, Allantoin, Grapefruit (Citrus Paradisi) Peel Extract, Orange (Citrus Aurantium Dulcis) Peel Extract, Cucumber (Cucumis Sativus) Fruit Extract, Matricaria (Chamomilla Recutita) Flower Extract, Aloe Barbadensis Leaf Extract, Beta-Glucan, Pentylene Glycol, Propanediol, PPG-26-Buteth-26, PEG-40 Hydrogenated Castor Oil, Caprylyl Glycol, Caprylic/Capric Triglyceride, Menthyl Lactate, Ethylhexylglycerin, Trisodium Ethylenediamine Disuccinate

Questions or comments?

1-888-DRMTLGY

MEDICAL GRADE SKIN CARE

2% BHA + 10% AHA

Made in the USA
www.DRMTLGY.com

DRMTLGY, LLC
Chatsworth, CA 91311